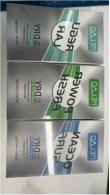 DRUG LABEL: ANTIPERSPIRANT DEODORANT
NDC: 83566-567 | Form: STICK
Manufacturer: Guangzhou Yilong Cosmetics Co., Ltd
Category: otc | Type: HUMAN OTC DRUG LABEL
Date: 20240807

ACTIVE INGREDIENTS: 3-HEXYLOXYPROPYLENE GLYCOL 5 g/100 g
INACTIVE INGREDIENTS: SODIUM HYDROXIDE 3 g/100 g; POLYSORBATE 20 2 g/100 g; WATER O-18 60 g/100 g; GLYCERIN 4 g/100 g; MPEG-400-GLY-NEU-GALNAC-THR 15 g/100 g; 17-HYDROXYSTEARIC ACID 4 g/100 g

ANTIPERSPIRANT DEODORANT

Active ingredients

Propylene Glycol 5%

Purpose

Antiperspirant fragrance

Uses

STEP1: Clean and thoroughly dry your skin.

STEP2: Twist the bottom of the product.

STEP3: Gently apply to the underarms or other desired areas.

Warning

For external use only

Stop use and ask a doctor if

rash occurs

Do not use

on damaged or broken skin

When using this product

keep out of eyes,rinse with water to remove

Keep out of reach of children.

If swallowed, get medical help or contact a Poison Control Center right away.

INACTIVE INGREDIENT

Water 60%

Stearic Acid 4%

Sodium Hydroxide 3%

Polysorbate 20 2%

Polysorbate 60 2%

Sucrose 2%

Tetrasodium EDTA 1%

Parfum 1%

Saururus Chinensis Leaf/Root Extract 0.4%

Taraxacum Officinale (Dandelion) Leaf Extract 0.37%

Stephania Tetrandra Root Extract 0.14% Cl 42090 0.08%

Cl 17200 0.01%

DOSAGE AND ADMINISTRATION

Squeeze out an appropriate amount of sunscreen and spread evenly on skin,